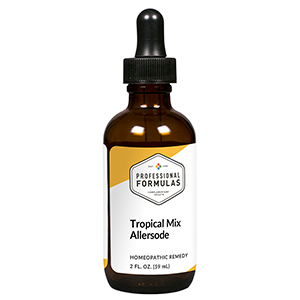 DRUG LABEL: Tropical
NDC: 63083-1022 | Form: LIQUID
Manufacturer: Professional Complementary Health Formulas
Category: homeopathic | Type: HUMAN OTC DRUG LABEL
Date: 20190815

ACTIVE INGREDIENTS: SUS SCROFA ADRENAL GLAND 6 [hp_X]/59 mL; CORTICOTROPIN 6 [hp_X]/59 mL; HISTAMINE DIHYDROCHLORIDE 12 [hp_X]/59 mL; BEEF LIVER 6 [hp_X]/59 mL; ACACIA 6 [hp_X]/59 mL; CYNODON DACTYLON WHOLE 6 [hp_X]/59 mL; XANTHIUM STRUMARIUM VAR. CANADENSE POLLEN 6 [hp_X]/59 mL; PLANTAGO LANCEOLATA LEAF 6 [hp_X]/59 mL; EUCALYPTUS GUM 6 [hp_X]/59 mL; POA PRATENSIS TOP 6 [hp_X]/59 mL; JUNIPERUS SCOPULORUM POLLEN 6 [hp_X]/59 mL; OLEA EUROPAEA FLOWER 6 [hp_X]/59 mL; AMARANTHUS HYBRIDUS LEAF 6 [hp_X]/59 mL; SYAGRUS ROMANZOFFIANA WHOLE 6 [hp_X]/59 mL; AMBROSIA ARTEMISIIFOLIA WHOLE 6 [hp_X]/59 mL; ATRIPLEX POLYCARPA WHOLE 6 [hp_X]/59 mL; WHITE MULBERRY 6 [hp_X]/59 mL
INACTIVE INGREDIENTS: ALCOHOL; WATER

ATH

ACTIVE INGREDIENTS

Adrenal 6X
ACTH 6X, 30X
Histaminum hydrochloricum 12X
Liver 6X, 12X
and all the following at 6X, 12X, 60X, 100X:
Acacia
Bermuda grass
Cocklebur
English plantain
Eucalyptus
Kentucky bluegrass
Mountain cedar
Olive pollen
Pigweed mix
Queen palm
Ragweed
Saltbush
White mulberry

QUESTIONS

Professional Formulas

PO Box 2034 Lake Oswego, OR 97035

INDICATIONS

For the temporary relief of runny nose, sneezing, itching of the nose or throat, and itchy, watery eyes due to sensitivity to common allergens in the tropics and Hawaii.*

PURPOSE

*Claims based on traditional homeopathic practice, not accepted medical evidence. Not FDA evaluated.

WARNINGS

In case of overdose, get medical help or contact a poison control center right away.

Keep out of the reach of children.

PREGNANCY OR BREAST FEEDING

If pregnant or breastfeeding, ask a healthcare professional before use.

DIRECTIONS

Place drops under tongue 30 minutes before/after meals. Adults and children 12 years and over: Take 10 to 15 drops up to 3 times per day. For desensitization, begin with 1 to 5 drops daily, increasing to the standard dose gradually to avoid symptom expression; after 1 to 3 months at the standard dose, decrease gradually to a maintenance dose of 10 to 15 drops weekly. Consult a physician for use in children under 12 years of age.

OTHER INFORMATION

Tamper resistant. If seal is broken, do not use. After opening, close container tightly and store at room temperature away from heat.

INACTIVE INGREDIENTS

20% ethanol, purified water.

LABEL

Est 1985

Professional Formulas

Complementary Health

Tropical

Homeopathic Remedy

2 FL. OZ. (59 mL)